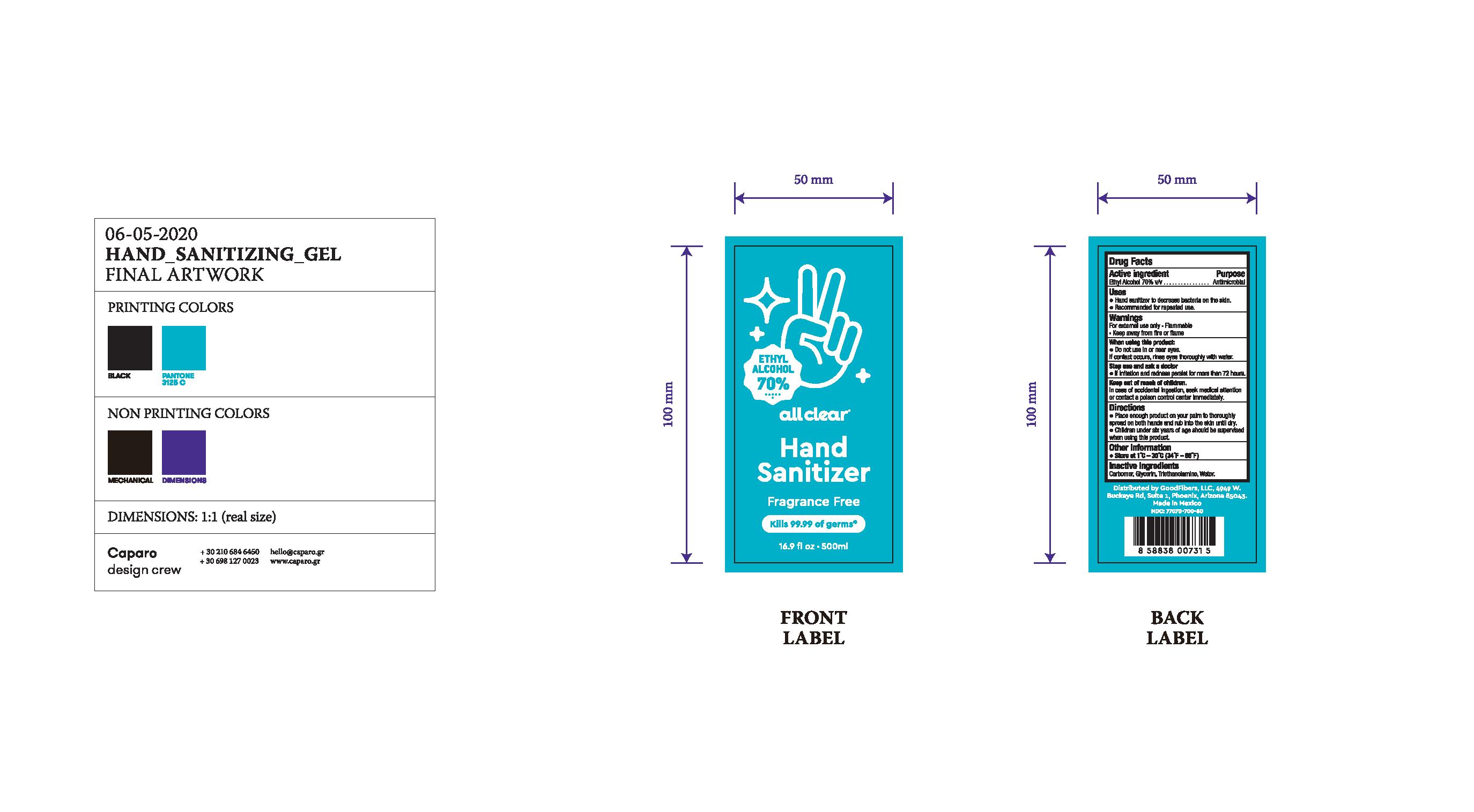 DRUG LABEL: Hand Sanitizer
NDC: 77070-700 | Form: GEL
Manufacturer: GoodFibers
Category: otc | Type: HUMAN OTC DRUG LABEL
Date: 20200729

ACTIVE INGREDIENTS: ALCOHOL 70 mL/100 mL
INACTIVE INGREDIENTS: WATER; GLYCERIN; TROLAMINE; ACRYLIC ACID

Alcohol

Active Ingredient

Ethyl Alcohol 70% v/v

Purpose

Antimicrobial

Uses

- Hand sanitizer to decrease bacteria on the skin
- Recommended for repeated use

Warnings

For external use only Flammable

- Keep away from fire or flame

When using

When using this product:

- Do not use in or near eyes

If contact occurs, rinse eyes thoroughly with water.

Stop use

Stop use and ask a doctor

- If irritation and redness persist for more than 72 hours.

Keep out of reach of children

In case of accidental ingestion, seek medical attention or contact a poison control centerimmediately

Directions

- Place enough product on your palm to thoroughly spread on both hands and rub into the skin until dry.
- Children under six years of age should be supervised when using this product.

Other information

- Store at 1oC - 30oC (34oF - 86oF)

Inactive ingredients

Carbomer, Glycerin, Triethanolamine, Water

PDP

Ethyl Alcohol

70%

all clear

Hand

Sanitizer

Fragrance Free

Kills 99.99 of germs

16.9 fl oz 500ml